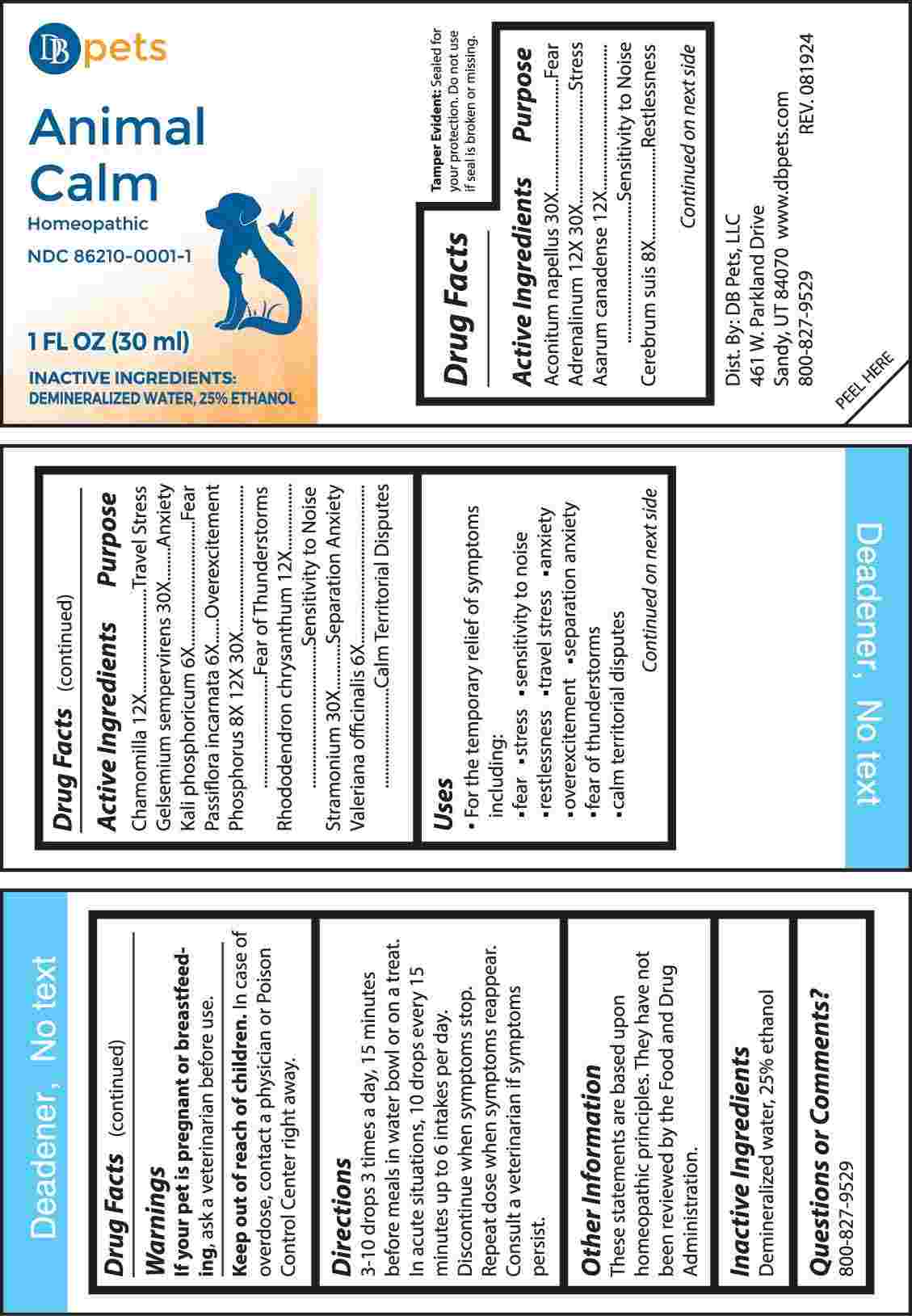 DRUG LABEL: Animal Calm
NDC: 86210-0001 | Form: LIQUID
Manufacturer: DB Pets LLC
Category: homeopathic | Type: OTC ANIMAL DRUG LABEL
Date: 20241001

ACTIVE INGREDIENTS: ACONITUM NAPELLUS WHOLE 30 [hp_X]/1 mL; EPINEPHRINE 12 [hp_X]/1 mL; ASARUM CANADENSE ROOT 12 [hp_X]/1 mL; SUS SCROFA CEREBRUM 8 [hp_X]/1 mL; MATRICARIA CHAMOMILLA WHOLE 12 [hp_X]/1 mL; GELSEMIUM SEMPERVIRENS ROOT 30 [hp_X]/1 mL; DIBASIC POTASSIUM PHOSPHATE 6 [hp_X]/1 mL; PASSIFLORA INCARNATA FLOWERING TOP 6 [hp_X]/1 mL; PHOSPHORUS 8 [hp_X]/1 mL; RHODODENDRON AUREUM LEAF 12 [hp_X]/1 mL; DATURA STRAMONIUM 30 [hp_X]/1 mL; VALERIAN 6 [hp_X]/1 mL
INACTIVE INGREDIENTS: WATER; ALCOHOL

DRUG FACTS:

ACTIVE INGREDIENTS:

Aconitum Napellus 30X, Adrenalinum 12X, 30X, Asarum Canadense 12X, Cerebrum Suis 8X, Chamomilla 12X, Gelsemium Sempervirens 30X, Kali Phosphoricum 6X, Passiflora Incarnata 6X, Phosphorus 8X, 12X, 30X, Rhododendron Chrysanthum 12X, Stramonium 30X, Valeriana Officinalis 6X.

PURPOSE:

Aconitum Napellus - Fear, Adrenalinum - Stress, Asarum Canadense – Sensitivity to Noise, Cerebrum Suis - Restlessness, Chamomilla – Travel Stress, Gelsemium Sempervirens - Anxiety, Kali Phosphoricum - Fear, Passiflora Incarnata - Overexcitement, Phosphorus – Fear of Thunderstorms, Rhododendron Chrysanthum – Sensitivity to Noise, Stramonium – Separation Anxiety, Valeriana Officinalis – Calm Territorial Disputes

USES:

• For the temporary relief of symptoms including:

•fear •stress •sensitivity to noise •restlessness •travel stress •anxiety

•overexcitement •separation anxiety •fear of thunderstorms •calm territorial disputes

These statements are based upon homeopathic principles. They have not been reviewed by the Food and Drug Administration.

WARNINGS:

If your pet is pregnant or breastfeeding, ask a veterinarian before use.

Keep out of reach of children. In case of overdose, contact a physician or Poison Control Center right away.

Tamper Evident: Sealed for your protection. Do not use if seal is broken or missing.

KEEP OUT OF THE REACH OF CHILDREN:

In case of overdose, contact a physician or Poison Control Center right away.

DIRECTIONS:

3-10 drops 3 times a day, 15 minutes before meals in water bowl or on a treat. In acute situations, 10 drops every 15 minutes up to 6 intakes per day. Discontinue when symptoms stop. Repeat dose when symptoms reappear. Consult a veterinarian if symptoms persist.

INACTIVE INGREDIENTS:

Demineralized water, 25% ethanol

QUESTIONS:

Dist. By: DB Pets, LLC

461 W. Parkland Drive

Sandy, UT 84070

www.dbpets.com

800-827-9529

PACKAGE LABEL DISPLAY:

DB pets

Animal Calm

Homeopathic

NDC 86210-0001-1

1 FL OZ (30 ml)